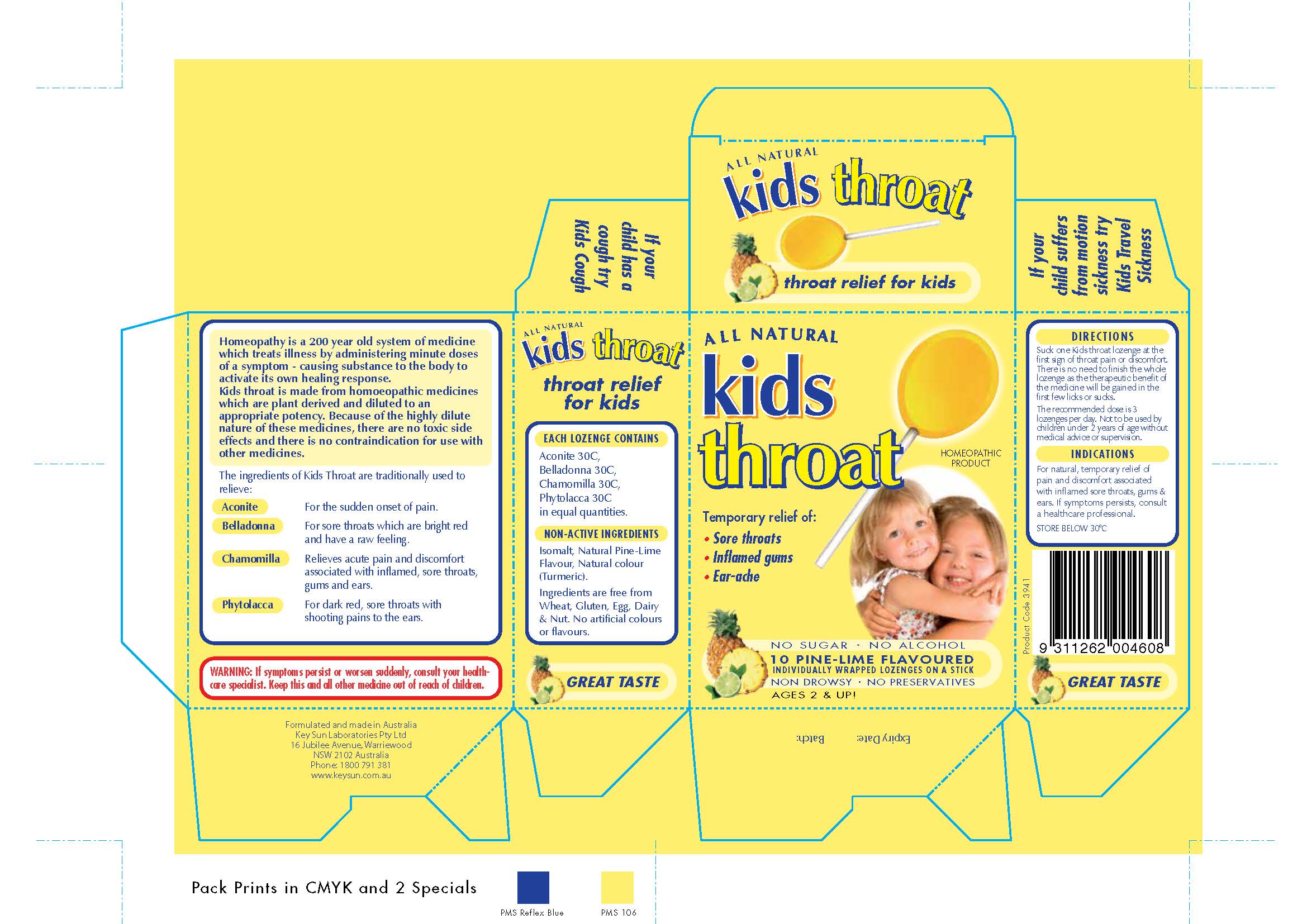 DRUG LABEL: kids throat
                
NDC: 64997-100 | Form: LOZENGE
Manufacturer: KEYSUN PTY. LIMITED Also Traded as KEYSUN LABORATORIES
Category: homeopathic | Type: HUMAN OTC DRUG LABEL
Date: 20140501

ACTIVE INGREDIENTS: ACONITUM NAPELLUS 30 [hp_X]/1 1; BELLADONNA LEAF 30 [hp_X]/1 1; MATRICARIA RECUTITA 30 [hp_X]/1 1; PHYTOLACCA AMERICANA ROOT 30 [hp_X]/1 1
INACTIVE INGREDIENTS: ISOMALT

Homeopathic Drug Facts

INACTIVE INGREDIENT

Non-Active Ingredients

Isomalt, Natural Pine-Lime

Flavour, Natural colour (Turmeric)

ACTIVE INGREDIENT

Each Lozenge Contains

Aconite 30C

Belladonna 30C

Chamomilla 30C

Phytolacca 30C

in equal quantities

PURPOSE

Indications

For natural, temporary relief of pain

and discomfort associated with inflamed sore throats, gums

and ears.

Warnings: If symptoms persist or worsen suddenly, consult

your health-care specialist.

KEEP OUT OF REACH OF CHILDREN

Keep this and all other medicine out of reach of children.

Directions

Suck one Kids throat lozenge at the

first sign of throat pain or discomfort.

There is no need to finish the whole

lozenge as the therapeutic benefit of the medicine

will be gained in the first few licks or sucks.

The recommended dose is 3 lozenges

per day. Not to be used by children under 2 years

of age without medical advice or supervision.

Indications

For natural, temporary relief of pain or discomfort

associated with inflamed sore throats, gums and

ears. If symptoms persists, consult a

healthcare professional.

STORAGE AND HANDLING

STORE BELOW 30 C